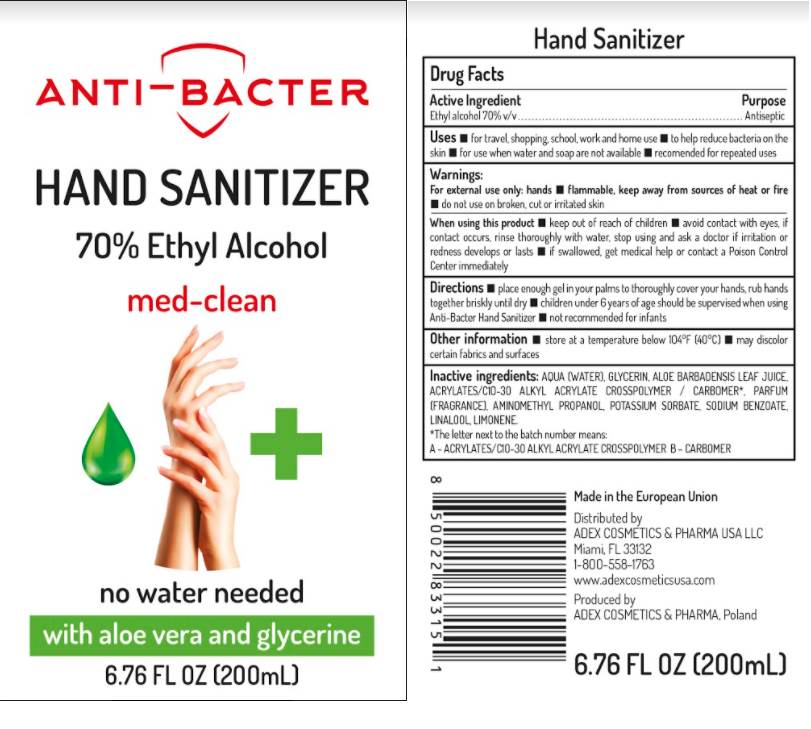 DRUG LABEL: Anti Bacter Hand Sanitizer Med Clean No Water Needed with Aloe Vera and Glycerine
NDC: 80457-001 | Form: GEL
Manufacturer: ADEX COSMETICS & PHARMA LESZEK SIERDZINSKI
Category: otc | Type: HUMAN OTC DRUG LABEL
Date: 20210325

ACTIVE INGREDIENTS: ALCOHOL 0.7 mL/1 mL
INACTIVE INGREDIENTS: WATER; GLYCERIN; ALOE VERA LEAF; ACRYLATES CROSSPOLYMER-6; AMINOMETHYLPROPANOL; POTASSIUM SORBATE; SODIUM BENZOATE; CARBOMER HOMOPOLYMER, UNSPECIFIED TYPE; LINALOOL, (+/-)-; LIMONENE, (+)-

Anti-Bacter Hand Sanitizer Med-Clean, 70% Ethyl Alcohol No Water Needed with Aloe Vera and Glycerine

Active Ingredient

Ethyl alcohol 70%

Purpose

Antiseptic

Uses

- for travel, shopping, school, work and home use
- to help reduce bacteria on the skin
- for use when water and soap are not available
- recommended for repeated uses

Warnings:

For External use only: hands

- flammable, keep away from sources of heat or fire
- do not use on broken, cut or irritated skin

When using this product

- avoid contact with eyes, if contact occurs, rinse thoroughly with water,

stop using and ak a doctor

if irritation or redness develops or lasts

keep out of reach of children

if swallowed, get medical help or contact a Poison Control Center immediately

Directions

- place enough gel in your palms to thoroughly cover your hands, rub hands together briskly until dry
- children under 6 years of age should be supervised when using Anti-Bacter Hand Sanitizer
- not recommended for infants

Other information

- store at a temperature below 104°F (40°C)
- may discolor certain fabrics and surfaces

Inactive ingredients:

Water, Glycerin, Aloe Barbadensis Leaf Juice, Acrylates/C10-30 Alkyl acrylate crosspolymer/carbomer*, mannitol, microcrystaline cellylose, hydroxypropyl methylcallulose, aloe barbadensis leaf juice powder, tocopheryl acecate, algin, parfum (fragrance), aminomethyl propanol, benzophenone-3, potassium sorbate, sodium benzoate, CI 74260, CI 77492 (Iron Oxide), CI 19140 (FD&C Yellow 5), CI 42090 (Blue 1).
*The letter next to the batch number means:
A- acrylates/C1O-3O alkyl acrylate crosspolymer B-carbomer